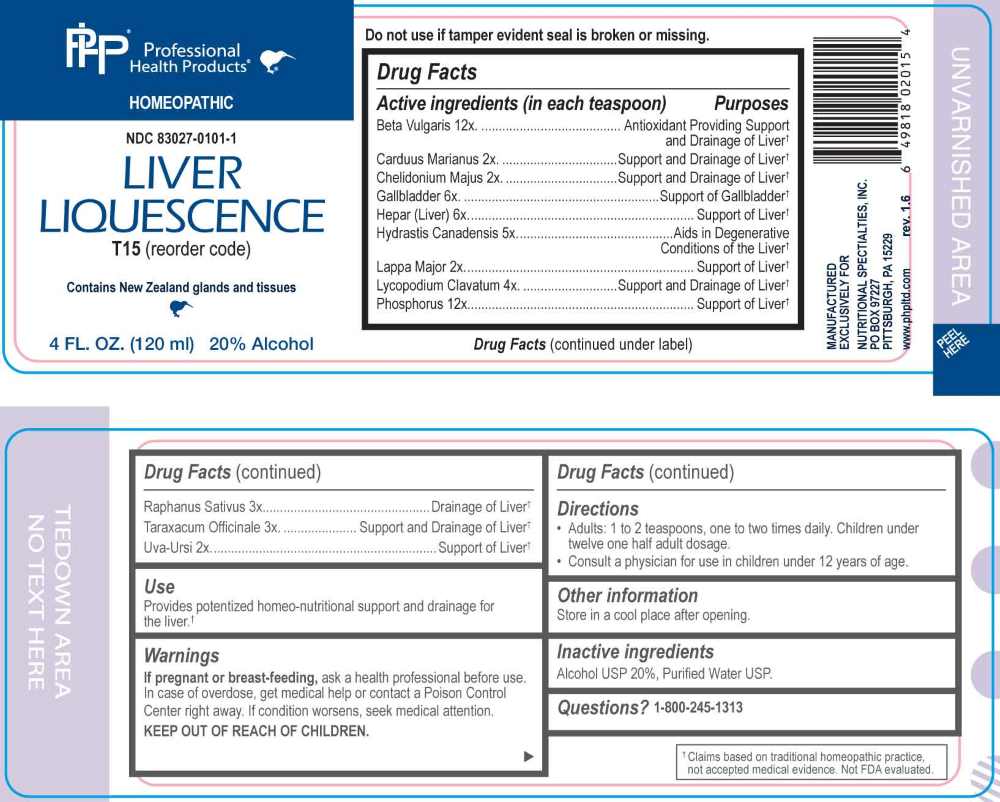 DRUG LABEL: Liver Liquescence
NDC: 83027-0101 | Form: LIQUID
Manufacturer: Nutritional Specialties, Inc.
Category: homeopathic | Type: HUMAN OTC DRUG LABEL
Date: 20251119

ACTIVE INGREDIENTS: MILK THISTLE 2 [hp_X]/1 mL; CHELIDONIUM MAJUS WHOLE 2 [hp_X]/1 mL; ARCTIUM LAPPA ROOT 2 [hp_X]/1 mL; ARCTOSTAPHYLOS UVA-URSI LEAF 2 [hp_X]/1 mL; RADISH 3 [hp_X]/1 mL; TARAXACUM OFFICINALE 3 [hp_X]/1 mL; LYCOPODIUM CLAVATUM SPORE 4 [hp_X]/1 mL; GOLDENSEAL 5 [hp_X]/1 mL; BOS TAURUS GALLBLADDER 6 [hp_X]/1 mL; HEPARIN, BOVINE 6 [hp_X]/1 mL; BETA VULGARIS WHOLE 12 [hp_X]/1 mL; PHOSPHORUS 12 [hp_X]/1 mL
INACTIVE INGREDIENTS: WATER; ALCOHOL

DRUG FACTS:

ACTIVE INGREDIENTS:

Beta Vulgaris 12X, Carduus Marianus 2X, Chelidonium Majus 2X, Gallbladder 6X, Hepar (Liver) 6X, Hydrastis Canadensis 5X, Lappa Major 2X, Lycopodium Clavatum 4X, Phosphorus 12X, Raphanus Sativus 3X, Taraxacum Officinale 3X, Uva-Ursi 2X.

PURPOSE:

Beta Vulgaris – Antioxidant Providing Support and Drainage of Liver,† Carduus Marianus – Support and Drainage of Liver,† Chelidonium Majus – Support and Drainage of Liver,† Gallbladder – Support of Gallbladder,† Hepar (Liver) – Support of Liver,† Hydrastis Canadensis – Aids in Degenerative,† Lappa Major – Support of Liver,† Lycopodium Clavatum – Support and Drainage of Liver,† Phosphorus – Support of Liver,† Raphanus Sativus – Drainage of Liver,† Taraxacum Officinale – Support and Drainage of Liver,† Uva-Ursi – Support of Liver†

†Claims based on traditional homeopathic practice, not accepted medical evidence. Not FDA evaluated.

USE:

Provides potentized homeo-nutritional support and drainage for the liver.†

†Claims based on traditional homeopathic practice, not accepted medical evidence. Not FDA evaluated.

WARNINGS:

If pregnant or breast-feeding, ask a health professional before use.

In case of overdose, get medical help or contact a Poison Control Center right away.

If condition worsens, seek medical attention.

KEEP OUT OF REACH OF CHILDREN

Do not use if tamper evident seal is broken or missing.

Store in a cool place after opening

KEEP OUT OF REACH OF CHILDREN:

In case of overdose, get medical help or contact a Poison Control Center right away.

DIRECTIONS:

• Adults: 1 to 2 teaspoons, one to two times daily. Children under twelve one half adult dosage.

Consult a physician for use in children under 12 years of age.

INACTIVE INGREDIENTS:

Alcohol USP 20%, Purified Water USP.

QUESTIONS:

MANUFACTURED EXCLUSIVELY FOR

NUTRITIONAL SPECIALTIES, INC.

PO BOX 97227

PITTSBURG, PA 15229

www.phpltd.com

1-800-245-1313

PACKAGE LABEL DISPLAY:

Professional

Health Products

HOMEOPATHIC

NDC 83027-0101-1

LIVER LIQUESCENCE

4 FL. OZ (120 ml)